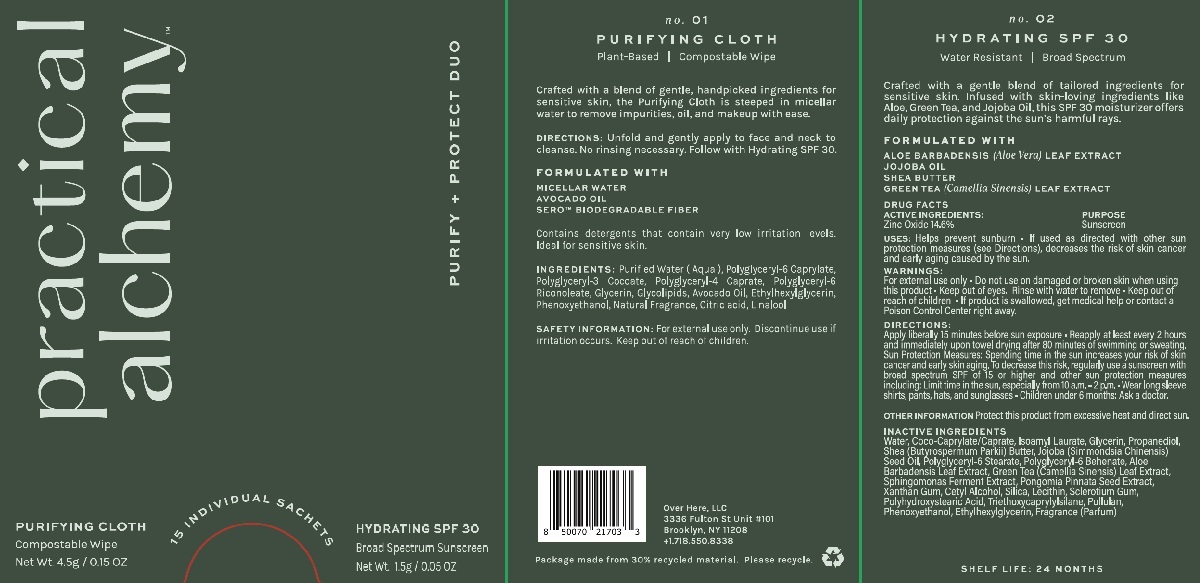 DRUG LABEL: Practical Alchemy Purify and Protect Duo
NDC: 84994-002 | Form: KIT | Route: TOPICAL
Manufacturer: Over Here, LLC
Category: otc | Type: HUMAN OTC DRUG LABEL
Date: 20250428

ACTIVE INGREDIENTS: ZINC OXIDE 14.6 g/100 g
INACTIVE INGREDIENTS: XANTHAN GUM; CETYL ALCOHOL; WATER; ISOAMYL LAURATE; JOJOBA OIL; GREEN TEA LEAF; PROPANEDIOL; POLYGLYCERYL-6 BEHENATE; TRIETHOXYCAPRYLYLSILANE; GLYCERIN; SHEA BUTTER; ETHYLHEXYLGLYCERIN; COCO-CAPRYLATE/CAPRATE; SCLEROTIUM GUM; SILICA; LECITHIN, SOYBEAN; POLYHYDROXYSTEARIC ACID (2300 MW); PULLULAN; PHENOXYETHANOL; ALOE VERA LEAF

Practical Alchemy - Purify + Protect Duo - Dual Sachet

ACTIVE INGREDIENTS:

Zinc Oxide 14.6%

WARNINGS:

For external use only • Do not use on damaged or broken skin when using this product • Keep out of eyes. Rinse with water to remove • Keep out of reach of children • If product is swallowed, get medical help or contact a Poison Control Center right away.

PURPOSE

Sunscreen

USES:

Helps prevent sunburn • If used as directed with other sun protection measures (see Directions), decreases the risk of skin cancer and early aging caused by the sun.

DIRECTIONS:

Apply liberally 15 minutes before sun exposure • Reapply at least every 2 hours and immediately upon towel drying after 80 minutes of swimming or sweating. Sun Protection Measures: Spending time in the sun increases your risk of skin cancer and early skin aging. To decrease this risk, regularly use a sunscreen with broad spectrum SPF of 15 or higher and other sun protection measures including: Limit time in the sun, especially from 10 a.m. - 2 pm • Wear long sleeve shirts, pants, hats, and sunglasses • Children under 6 months: Ask a doctor.

OTHER INFORMATION

Protect this product from excessive heat and direct sun.

INACTIVE INGREDIENTS

Water, Coco-Caprylate/Caprate, Isoamyl Laurate, Glycerin, Propanediol, Shea (Butyrospermum Parkii) Butter, Jojoba (Simmondsia Chinensis) Seed Oil, Polyglyceryl-6 Stearate, Polyglycerl-6 Behenate, Aloe Barbadensis Leaf Extract, Green Tea (Camellia Sinensis) Leaf Extract,Sphingomonas Ferment Extract, Pongomia Pinnata Seed Extract, Xanthan Gum, Cetyl Alcohol, Silica, Lecithin, Sclerotium Gum, Polyhydroxystearic Acid, Triethoxycaprylylsilane, Pullulan, Phenoxyethanol, Ethylhexylglycerin, Fragrance (Parfum)